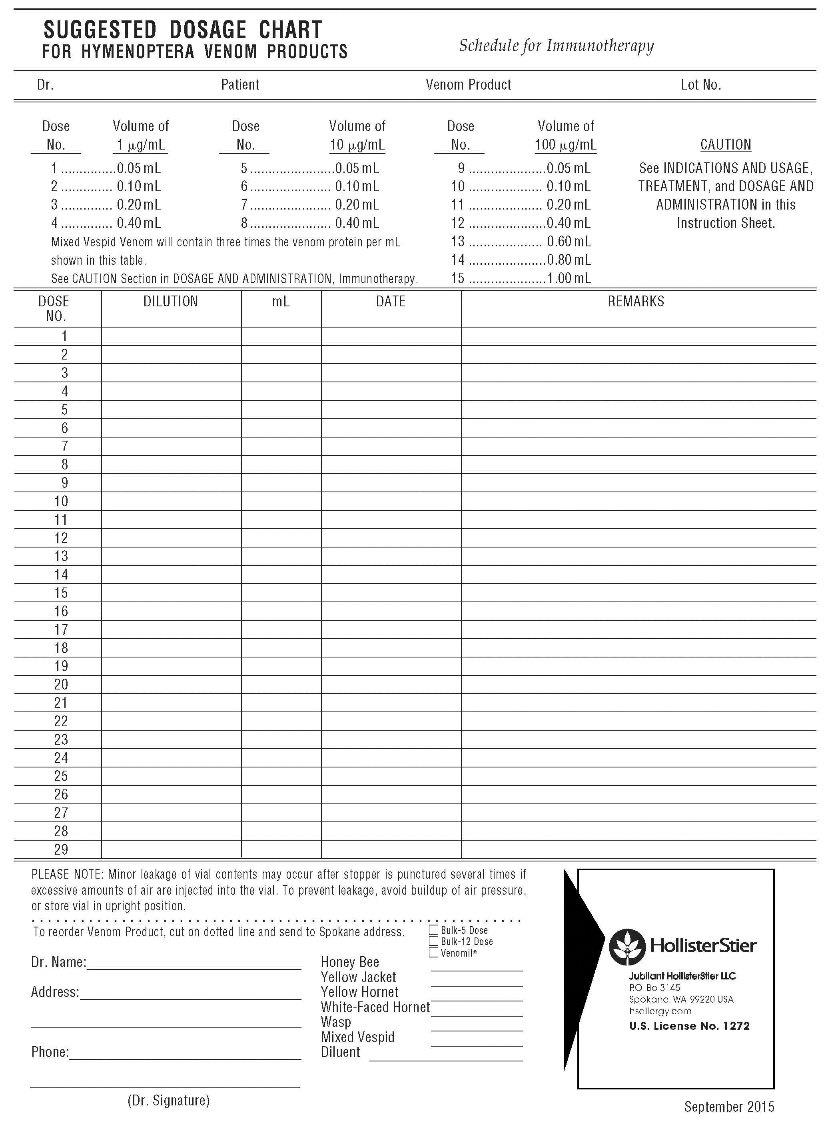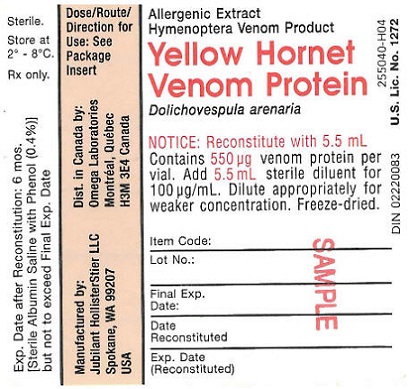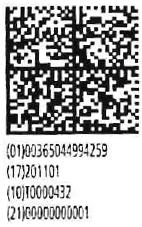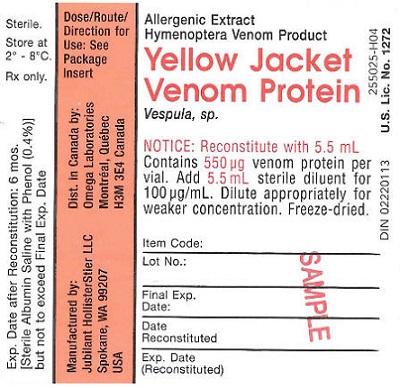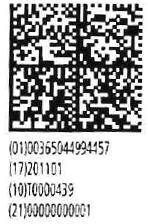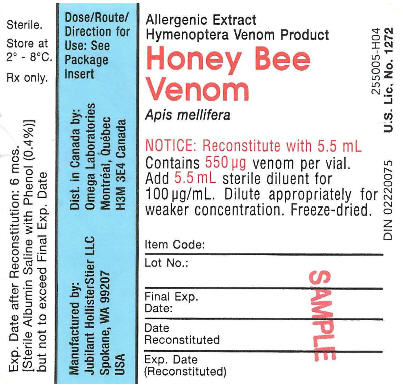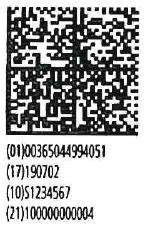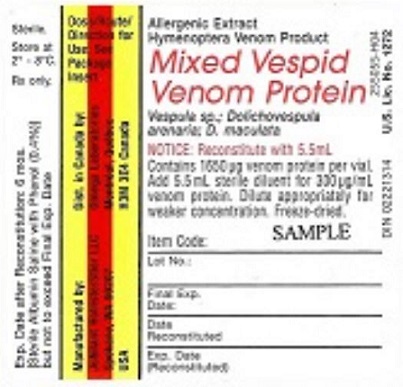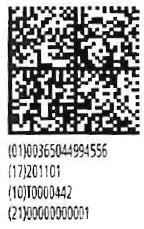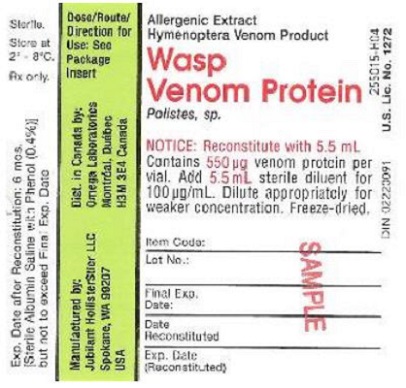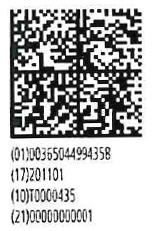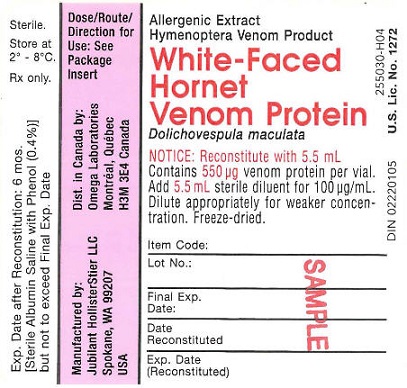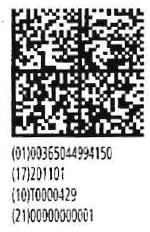 DRUG LABEL: Honey Bee Hymenoptera Venom Multidose
NDC: 65044-9940 | Form: INJECTION, POWDER, LYOPHILIZED, FOR SOLUTION
Manufacturer: Jubilant HollisterStier LLC
Category: other | Type: STANDARDIZED ALLERGENIC
Date: 20251119

ACTIVE INGREDIENTS: APIS MELLIFERA VENOM 100 ug/1 mL
INACTIVE INGREDIENTS: MANNITOL

Instructions and Dosage Schedule for Allergenic Extracts Hymenoptera Venom Products (Honey Bee, Yellow Jacket, Yellow Hornet, White-Faced Hornet, Wasp, and Mixed Vespid)

WARNINGS

This product is intended for use only by licensed medical personnel experienced in administering allergenic extracts and trained to provide immediate emergency treatment in the event of a life-threatening reaction. Hymenoptera venom extracts may potentially elicit a severe life-threatening systemic reaction, rarely resulting in death. (1) Therefore, emergency measures and personnel trained in their use must be available immediately in the event of such a reaction. Patients should be instructed to recognize adverse reaction symptoms, observed in the office for at least 30 minutes after skin testing or treatment, and cautioned to contact the physician's office if symptoms occur. See ADVERSE REACTION, Section 3, of the instruction for information regarding adverse event reporting.
All patients should have available an Emergency Anaphylaxis Kit containing epinephrine and be instructed in its use for emergency treatment of possible systemic reactions occurring at times after the patient has departed the testing or treatment premises. Patients with cardiovascular diseases and/or pulmonary diseases such as symptomatic unstable, steroid-dependent asthma, and/or those who are receiving cardiovascular drugs such as beta blockers, may be at higher risk for severe adverse reactions. These patients may also be more refractory to the normal allergy treatment regimen. Patients should be treated only if the benefit of treatment outweighs the risks. (1)
Patients on beta blockers may be more reactive to allergens given for testing or treatment and may be unresponsive to the usual doses of epinephrine used to treat allergic reactions. (2)
Immunotherapy for insect sting allergy should be given to those patients who have experienced significant systemic reactions (for detailed description of symptoms see INDICATIONS AND USAGE and ADVERSE REACTIONS) from insect stings and who demonstrate hypersensitivity by skin testing with these products. The only approved method for diagnosing insect sting allergic patients for immunization is by skin testing.
This product must never be injected intravenously.
Refer also to CONTRAINDICATIONS, WARNINGS, PRECAUTIONS, ADVERSE REACTIONS and OVERDOSAGE for further discussion.

DESCRIPTION

Hymenoptera Venom Products available are sterile freeze-dried venom of Honey Bee (Apis mellifera) and venom protein of Yellow Jacket (Vespula sp.), Yellow Hornet (Dolichovespula arenaria), White-Faced Hornet (Dolichovespula maculata) and Wasp (Polistes sp.). Mixed Vespid venom protein (Yellow Jacket, Yellow Hornet and White-Faced Hornet) is also available.
The reconstituted single venom products are intended for subcutaneous injection for immunotherapy and percutaneous use for diagnosis. The Mixed Vespid venom protein is for immunotherapy only, not for diagnosis. Diagnosis should be based on individual venoms.
Because of the difficulty in collecting all species of Yellow Jacket and Wasp, the venom raw materials for these two insects may vary in species composition from lot to lot. A listing of the exact species content for any particular lot of Yellow Jacket or Wasp venom protein may be obtained by calling Technical Services at Jubilant HollisterStier LLC, (800) 992-1120.
Final containers of sterile freeze-dried venom products are sealed under vacuum. This will result in the diluting fluid being forcibly drawn into the sealed vial when the syringe needle penetrates the seal during reconstitution. See PRECAUTIONS.
When the sterile freeze-dried Honey Bee venom is reconstituted with 5.5 mL of sterile fluid, the resulting solution will contain 100 micrograms of venom per mL (100 µg/mL) plus 7.7 milligrams of mannitol per mL. When freeze-dried Yellow Jacket, Yellow Hornet, White-Faced Hornet and Wasp venom proteins are reconstituted with 5.5 mL of fluid, the resulting solution will contain 100 micrograms of venom protein per mL (100 µg/mL) plus 7.7 milligrams of mannitol per mL and trace amounts of sodium chloride, potassium chloride, acetic acid and beta-alanine. When the freeze-dried Mixed Vespid venom protein is reconstituted with 5.5 mL of fluid, the resulting solution contains 300 micrograms of venom protein per mL (300µg/mL) plus 23.1 milligrams of mannitol per mL and trace amounts of sodium chloride, potassium chloride, acetic acid and beta-alanine. Mannitol is used as an excipient.
These freeze-dried products can be reconstituted in Sterile Albumin Saline with Phenol (which contains 0.9% NaCl, 0.4% phenol and 0.03% normal human serum albumin) to a concentration of 100 µg/mL (300 µg/mL for Mixed Vespid Venom Protein). Dilutions of this concentration should be made only with Sterile Albumin-Saline with Phenol (0.4%). See DOSAGE AND ADMINISTRATION for details of dilutions for diagnosis and treatment.
Space is provided on the container label to record the date (month, day, year) venom is reconstituted. Refer to dating period shown under PRECAUTIONS. At the time of reconstitution, write the calculated reconstituted product expiration date (month, day, year) on the vial label in the space provided.

CLINICAL PHARMACOLOGY

Diagnosis
Diluted solutions of stinging insect venoms injected intradermally will produce wheal and erythema reactions in patients who have significant IgE-mediated, Type I immediate hypersensitivity to stings of these insects.
Treatment
Repeated injections of increasing doses of insect venom extracts have been shown to ameliorate the intensity of allergic symptoms upon subsequent insect stings.(3, 4)
The mechanism by which hyposensitization is achieved is not known completely. IgG antibodies (blocking antibodies) appear in the serum of patients treated with injected venom. No direct relationship has been identified between the level of blocking antibody (or the ratio of blocking antibody to IgE antibody directed to the same venom antigens) and the degree of hyposensitization. However, patients who show protection from symptoms after stings have been found to have significant levels of specific blocking antibody.(3, 4)
Initially, after a period of immunotherapy with specific venom antigens, levels of IgE antibody may increase.(4) However, from studies carried out with other venom preparations, these levels are reported to decline after a time.(5)After maintenance level has been reached and maintained, symptoms after stings have been shown to decrease considerably. (3, 4)
It is not known if skin-sensitizing antibody can be eradicated or if the patient can be entirely cured, nor is it known how long immunotherapy must be continued.
In a clinical study with Jubilant HollisterStier venom products, injections (using the Suggested Dose Schedule under DOSAGE AND ADMINISTRATION) were given once per week at one study center, and twice or more per week at another center. (4) (For further discussion, see below). It must be considered important to achieve the 100 µg per venom maintenance dose (the maintenance dose for Mixed Vespid venom protein is 300 µg) , since there are no data on effectiveness of maintenance levels below 100 µg per venom.
In the clinical trial, 97% of patients at the maintenance dosage (100 µg per venom) showed no systemic reaction following an insect sting challenge. (4) The remaining 3% had a milder reaction than noted prior to treatment. The patients in this study reached maintenance (100 µg per venom) usually within 2½-3½ months after beginning therapy. (4) Whether efficacy of therapy is influenced by the time required to reach maintenance has not yet been determined.
Large local reactions occurred in approximately 60% of the patients given immunotherapy. Some form of systemic response occurred, often repeatedly, in one-third of the patients treated in the clinical trial. (4) Only one systemic response occurred on the first dose given. The rest occurred at various times in the course of immunotherapy. Some systemic manifestations may have occurred because of the patient's apprehension, and did not require treatment. Approximately one-fourth of the patients experiencing systemic responses were given some form of specific therapy (epinephrine, theophylline, or metaproteranol), some on several occasions. (4)
In deciding the criteria for proceeding from dose to dose of the Suggested Dose Schedule (see DOSAGE AND ADMINISTRATION), the results of the clinical study (4) should be considered. A study center "A" reporting the least number of systemic reactions during pre-maintenance treatment held the dose constant in most of the cases where significant local reactions occurred. With the systemic reactions reported, this center held the dose the same in approximately 80% of the incidences. The treatment injections were given at this center usually once per week, and if a patient missed an appointment, the next dose was often the same as the preceding dose (depending on the previous reactivity of the patient). Patients treated at this center reached maintenance in an average of 17-19 visits.
Another study center "B", reporting a higher incidence of systemic reactions, was more regimented in following the Suggested Dose Schedule. This center reduced or held the dose the same in less than 10% of the cases reporting significant local reactions. With the systemic reactions reported, this center held the dose the same or reduced the dosage in approximately 20% of the cases. At this center, more than one injection per week was given at the outset as circumstances and sensitivity allowed. Patients treated at this center reached maintenance in an average of 14 visits.
Following the achievement of maintenance level (100 µg per venom), approximately 80% or more patients were given a second maintenance injection at a 1-week interval. The third maintenance injection was usually (in approximately 60% of the patients) at a 2- week interval. The next injection was usually within 3 weeks, and thereafter, the patients were injected for ongoing maintenance at approximately monthly intervals. (4)

INDICATIONS AND USAGE

Insect stings may induce a wide range of allergic symptoms in sensitive patients. A normal sting response is initial burning or stinging pain that may be intense and last several minutes to an hour or more. There is usually some local swelling coming on immediately and persisting for several days. The location of the sting has considerable influence on the intensity of the pain and extent of swelling. Stings on the fingers or feet produce much pain, but less swelling; whereas a sting on the head or face produces extensive swelling with variable pain.
Local reactions coming on rapidly and larger than the usual local reaction, particularly if the swelling spans both adjacent joints on the extremities, can indicate hypersensitivity. Systemic symptoms come on shortly after the sting, often within seconds to minutes. Symptoms may range from generalized flushing, itching, redness, diffuse swelling of the skin or urticarial wheals, abdominal cramps, nausea, vomiting, or incontinence of urine or stool, to faintness, blurring or loss of vision, unconsciousness, seizures, respiratory or cardiac arrest, or death. Later reactions may consist of fever, achiness, malaise, joint swelling, urticaria or other signs of vascular damage typical of serum sickness, a Type III reaction. Typical delayed Type IV reactions may also occur.(6)
Rarely, other types of severe reactions to insect stings have been reported.(6) These include serum sickness, hematologic abnormalities, and neurological disorders commencing some time after a sting, and not associated with anaphylactoid reactions. These patients are not candidates for immunotherapy using insect venoms.

(1) Diagnosis
Skin testing with insect venoms is useful to demonstrate the presence of IgE antibodies which account for the patient's symptoms.(3) Patients are seldom able to identify the insect which stung them, so skin testing is used to determine the insect culprit. Dilutions of these venom products will help judge the sensitivity of the patient and whether the patient should be treated.(7)
It is not absolutely known what levels (micrograms) of venom, that elicit positive skin tests, are diagnostic of clinical sensitivity. However, patients with a history of reactions (any of three types: generalized urticaria or angioedema; respiratory difficulty due either to laryngeal edema or to bronchospasm; or vascular collapse, with or without loss of consciousness) to previous stings and a positive skin test to a venom intradermal injection of approximately 1 µg/mL had about a 60% chance of reacting again when stung by the same insect. These patients should receive venom immunotherapy.(3)
Patients with a history of reaction (any of the three reaction types described above) to previous stings, but did not demonstrate a positive skin test reaction to venom, were considered in a previous study not to be clinically sensitive, and were not treated.(3) We cannot recommend treatment for such patients.
Another study demonstrated false positive reactions when skin testing with venom concentrations of 10 µg/mL and 100 µg/mL was carried out.(8) Thus there can be a nonspecific skin test reaction potentially due to the pharmacological action of the venom at higher concentrations.
The best statement that can be made, at present, is that patients with significant positive history (reactions of the three types described above) following an insect sting, and who do react with a positive skin test to a venom concentration of 1 µg/mL or less, are recommended for treatment. Patients who have the history described above, but do not react to a 1 µg/mL intradermal venom skin test, cannot be recommended for treatment. At present, the data does not exist to determine whether a patient who might react to a higher concentration, e.g., 2-10 µg/mL, is at risk from a subsequent sting or not. Since it is not known if sting-sensitive patients who subsequently lose their IgE anti-venom antibody can be re-sensitized by further stings, it is advisable to retest these patients after any subsequent stings.(3)However, since the level of venom-specific IgE may fall to low levels briefly after a sting, patients should not be re-tested until 2 to 4 weeks after any sting.

(2) Treatment
Immunotherapy is indicated for those patients diagnosed as sensitive (see Diagnosis above) and is accomplished by using graduated dilutions of the appropriate insect venom or venoms to control the severity of the patient's symptoms from subsequent stings.
Increasing doses of venom are given at intervals, dependent on the patient's ability to tolerate the venom, until a maintenance dosage (100 µg venom is recommended or 300 µg in the case of Mixed Vespid venom protein) is reached and maintained.
Venom sensitivity differs for individual patients, thus it is not possible to provide a dosage schedule that is universally suited to all patients. The dosage schedule shown under DOSAGE AND ADMINISTRATION is a summary of the schedule used in clinical trials of our product and found suitable for the majority of patients. In highly sensitive patients, the physician may be required to use a modified dose schedule, based on the patient's sensitivity to and tolerance of the injections. Lower initial doses and smaller dosage increments than shown under DOSAGE AND ADMINISTRATION may be necessary.

CONTRAINDICATIONS

There are no known absolute contraindications to immunotherapy using Hymenoptera Venom Products. See also PRECAUTIONS and WARNINGS.
Patients showing negative intradermal skin tests to specific venoms at 1 µg/mL are not recommended for venom treatment. Any injections, including immunotherapy, should be avoided in patients with a bleeding tendency.
Patients with cardiovascular diseases and/or pulmonary diseases such as symptomatic unstable, steroid-dependent asthma, and/or those who are receiving cardiovascular drugs such as beta blockers, may be at higher risk for severe adverse reactions. These patients may also be more refractory to the normal allergy treatment regimen. Patients should be treated only if the benefit of treatment outweighs the risks.(1) Patients on beta blockers may be more reactive to allergens given for testing or treatment and may be unresponsive to the usual doses of epinephrine used to treat systemic reactions. (2)
Since there are differences of opinion concerning the possibility of routine immunizations exacerbating autoimmune diseases, immunotherapy should be given cautiously to patients with other immunologic diseases and only if the risk from insect stings is greater than the risk of exacerbating the underlying disorder.

WARNINGS

See WARNINGS box at the beginning of this Instruction Sheet. See alsoPRECAUTIONS. Venom extract must be temporarily withheld from patients or the dose adjusted downward if any of the following conditions exist: (1) severe symptoms of rhinitis and/or asthma; (2) infection or flu accompanied by fever; (3) any evidence of an excessively large local or any generalized reaction during the initial stages of immunotherapy, or during maintenance therapy; and/or (4) insect sting prior to scheduled injection. Do not administer venom injections during a period of symptoms following an insect sting or on the day the patient received an insect sting, since this could result in an allergen load that exceeds the patient's tolerance.
THE CONCENTRATE MUST NOT BE INJECTED AT ANY TIME UNLESS TOLERANCE HAS BEEN ESTABLISHED. DILUTE CONCENTRATED EXTRACTS WITH STERILE ALBUMIN SALINE WITH PHENOL (0.4%) FOR SKIN TESTING AND IMMUNOTHERAPY. INJECTIONS MUST NEVER BE GIVEN INTRAVENOUSLY. Subcutaneous injection is recommended. Intracutaneous or intramuscular injections may produce large local reactions or be excessively painful. AFTER INSERTING NEEDLE SUBCUTANEOUSLY, BUT BEFORE INJECTING, ALWAYS WITHDRAW THE PLUNGER SLIGHTLY. IF BLOOD APPEARS IN THE SYRINGE, CHANGE NEEDLE AND GIVE THE INJECTION IN ANOTHER SITE.
Patients with hypersensitivity to insect venom who undergo desensitization treatment while under concomitant therapy with ACE (angiotensin-converting enzyme) inhibitors, may have an increased risk of life-threatening anaphylactic reactions.(9) Patients without insect venom hypersensitivity, who take ACE inhibitors, and are stung by insects such as bee or wasp, can show such reactions as well.(10)
Two patients undergoing desensitization treatment with Hymenoptera Venom while receiving ACE inhibitors sustained life-threatening anaphylactoid reactions. In the same patients, these reactions were avoided when ACE inhibitors were temporarily withheld, but they reappeared upon inadvertent rechallenge.(11)
IF CHANGING TO A DIFFERENT LOT OR A FRESHLY RECONSTITUTED VIAL OF VENOM EXTRACT: All extracts lose potency over time, and a fresh extract could have an effective potency that is substantially greater than that of the old extract. The first dose from the new vial should not exceed 50% of the previous dose. IF THE VENOM EXTRACT PREVIOUSLY USED WAS FROM ANOTHER MANUFACTURER: Since manufacturing processes and sources of raw materials differ among manufacturers, the interchangeability of extracts from different manufacturers cannot be insured. The starting dose of the venom extract therefore should be greatly decreased even though the extract is the same formula and dilution. In general, a dose reduction to 50% of the previous product dose should be adequate, but each situation must be evaluated separately considering the patient's history of sensitivity, tolerance of previous injections, and other factors. If the patient tolerates a 50% decrease, the next dose could be raised to the previous dose amount. If the decrease is greater than 50%, the next dose would need to be determined by the allergist, depending on the situation. Dose intervals should not exceed one week when rebuilding dose. See DOSAGE AND ADMINISTRATION.
IF A PROLONGED PERIOD OF TIME HAS ELAPSED SINCE THE LAST INJECTION: Patients may lose tolerance for allergen injections during prolonged periods between doses. The duration of tolerance is an individual characteristic and varies from patient to patient. In general, the longer the lapse in the injection schedule, the greater dose reduction required. If the interval since last dose is over four weeks, perform skin tests to determine starting dose. See DOSAGE AND ADMINISTRATION.
IF THE PREVIOUS EXTRACT WAS OUTDATED: The dating period for allergenic extracts indicates the time that they can be expected to remain potent under refrigerated storage conditions (2° - 8°C). During the storage of extracts, even under ideal conditions, some loss of potency occurs. For this reason, extracts should not be used beyond their expiration date. If a patient has been receiving injections of an outdated extract, s/he may experience excessive local or systemic reactions when changed to a new, and possibly more potent extract. In general, the longer the material has been outdated, the greater the dose reduction necessary when starting the fresh extract.
Proper selection of the dose and careful injection should prevent most systemic reactions. It must be remembered, however, that allergenic extracts are highly potent in sensitive individuals and that systemic reactions of varying degrees of severity may occur, ranging from mild to life-threatening anaphylaxis, or even death, as described under INDICATIONS AND USAGE and ADVERSE REACTIONS. Patients should be informed of this, and the warnings and precautions should be discussed prior to immunotherapy. See PRECAUTIONS below. Systemic reactions should be treated as indicated in ADVERSE REACTIONS.

PRECAUTIONS

(1) GENERAL

The presence of asthmatic signs and symptoms appear to be an indicator for severe reactions following allergy injections. An assessment of airway obstruction either by measurement of peak flow or an alternate procedure may provide a useful indicator as to the advisability of administering an allergy injection.(1, 12-16)

Concentrated extracts must not be injected unless tolerance has been established.

Diluting fluid should be forcibly drawn into the sealed vial when the syringe needle penetrates the seal during reconstitution. Failure of this to occur for a particular vial indicates possible loss of vacuum. Vials without vacuum should be returned to the manufacturer.

Record date of reconstitution and expiration date of reconstituted product in the space provided on the product label. Date of expiration after reconstitution must not exceed the Final Expiration Date indicated on the container label. (See table below for expiration dates, including dilutions.)

Maintain stock solutions and dilutions constantly at 2° - 8°C.

Venom Concentration | Diluent | Recommended Expiration Date*
100 µg/mL | Albumin Saline with Phenol (0.4%) | 6 months
10 µg/mL | Albumin Saline with Phenol (0.4%) | 1 month
1 µg/mL | Albumin Saline with Phenol (0.4%) | 1 month
0.1 µg/mL | Albumin Saline with Phenol (0.4%) | 14 days
Less than 0.1 µg/mL | Albumin Saline with Phenol (0.4%) | Prepare Fresh Daily

* But not to exceed Final Expiration Date included on the container label.

Sterile solutions, vials, syringes, etc., should be used and aseptic precautions observed in making dilutions.

To avoid cross-contamination, do not use the same needle to withdraw materials from vials of more than one extract, or extract followed by diluent.

A sterile tuberculin syringe, with a needle at least 5/8" long and graduated in 0.01 mL units, should be used to carefully measure each dose from the appropriate dilution. Aseptic techniques should always be employed when injections are being administered.

A separate sterile syringe should be used for each patient to prevent transmission of hepatitis and other infectious agents from one person to another.

Patient reactions to previous injections should be reviewed before each new injection so that dose can be adjusted accordingly. See ADVERSE REACTIONS and WARNINGS.

Rarely, a patient is encountered who develops systemic reactions to minute doses of allergen and does not demonstrate increasing tolerance to injections after several months of treatment. It is suggested that if systemic reactions or excessive local responses occur persistently at very small doses, efforts at immunotherapy should be stopped.

PATIENTS SHOULD BE OBSERVED IN THE OFFICE FOR AT LEAST 30 MINUTES AFTER SKIN TESTING AND AFTER EACH TREATMENT INJECTION. Most severe reactions will occur within this time period, and rapid treatment measures should be instituted. See ADVERSE REACTIONS for such treatment measures.

(2) INFORMATION FOR PATIENTS

Patients should be instructed in the recognition of adverse reactions to immunotherapy, and in particular, to the symptoms of shock. (See WARNINGS box at the beginning of this Instruction Sheet.) Patients should be made to understand the importance of a 30 minute observation period following skin testing or therapeutic injections, and be cautioned to return to the office promptly if symptoms occur after leaving. Patients should be instructed in the use of, and have available, an Emergency Anaphylaxis Kit for self-administration of epinephrine. Patients must be instructed to report any insect stings that have occurred, since a venom injection should not be given on the same day as the sting, nor during a time when the patient is still experiencing symptoms from the sting.

(3) DRUG INTERACTIONS

Patients with cardiovascular diseases and/or pulmonary diseases such as symptomatic, unstable, steroid-dependent asthma, and/or those who are receiving cardiovascular drugs such as beta blockers, may be at higher risk for severe adverse reactions. These patients may also be more refractory to the normal allergy treatment regimen. Patients should be treated only if the benefit of treatment outweighs the risks. (1) Patients on beta blockers may be more reactive to allergens given for testing or treatment and may be unresponsive to the usual doses of epinephrine used to treat allergic reactions. (2) See WARNINGS section regarding concurrent treatment with ACE inhibitors. Certain medications may lessen the skin test wheal and erythema responses elicited by allergens and histamine for varying time periods. Conventional antihistamines should be discontinued at least 5 days before skin testing. Long acting antihistamines should be discontinued for at least 3 weeks prior to skin testing. (17) Topical steroids should be discontinued at the skin test site for at least 2-3 weeks before skin testing. (17, 18)
Tricyclic antidepressants, such as doxepin, should be withheld for at least 7 days before skin testing. (19) Topical local anesthetics may suppress the flare responses and should be avoided on skin test sites. (20) When using other drugs in patients receiving allergenic extracts, always consult the product labeling of the other drugs to determine any possible interaction with use of allergenic extracts, and specifically with stinging insect (Hymenoptera) venom extracts.

(4) CARCINOGENESIS, MUTAGENESIS, IMPAIRMENT OF FERTILITY

Long-term studies in animals have not been conducted with allergenic extracts to determine their potential for carcinogenicity, mutagenicity, or impairment of fertility.

(5) PREGNANCY

(12,21)
Animal reproduction studies have not been conducted with Hymenoptera Venom Products. It is also not known whether Hymenoptera Venom Products can cause fetal harm when administered to a pregnant woman or can affect reproduction capacity. Hymenoptera Venom Products should be given to a pregnant woman only if clearly needed. On the basis of histamine's known ability to contract uterine muscle, theoretically, a systemic reaction, whether occurring from insect sting or from venom skin testing or treatment dose, should be avoided. Therefore, the physician must carefully consider the benefit-to-risk ratio, to both patient and fetus, of continuing venom immunotherapy during pregnancy, or performing venom skin testing, and especially of initiating a venom immunotherapy program where there is a possibility that the patient may not be able to reach the recommended maintenance dose without significant risk of a systemic reaction.

(6) NURSING MOTHERS

There are no current studies on secretion of the allergenic extract components in human milk or effect on the nursing infant. Because many drugs are excreted in human milk, caution should be exercised when allergenic extracts are administered to a nursing woman.

(7) PEDIATRIC USE

Since dosage for the pediatric population is the same as for adults, the larger volumes of solution may produce excessive discomfort. Therefore, in order to achieve the total dose required, the volume of the dose may need to be divided into more than one injection per visit. A study done in children ages 4 to 17 showed no special problems with venom immunotherapy in this population. (22)

(8) GERIATRIC USE

The reactions from immunotherapy can be expected to be the same in elderly patients as in younger ones. Elderly patients may be more likely to be on medication that could block the effect of epinephrine which could be used to treat serious reactions, or they could be more sensitive to the cardiovascular side effect of epinephrine because of pre-existing cardiovascular disease. (23)

ADVERSE REACTIONS

Physicians administering Hymenoptera Venom testing or treatment materials should be experienced in the treatment of severe systemic reactions (seeWARNINGS Box at the beginning of this Instruction Sheet).
(1) Local Reactions
Some erythema, swelling or pruritis at the site of injection are common, the extent varying with the patient. Excessively large, painful or persistent local reactions can occur from skin tests or immunotherapy. Frequent application of cold, wet dressings to the area and/or the use of oral antihistamines will ameliorate the discomfort. Reactions usually subside in 24-36 hours. Large local reactions occurred in approximately 60% of the patients given immunotherapy in a clinical study. None of the local reactions required specific treatment; however, subsequent injections in many instances were held to the previous dose or a reduced dose. Some patients had repeated large local reactions that slowed the increase in the immunotherapy dose.(4) See CLINICAL PHARMACOLOGY and DOSAGE AND ADMINISTRATION section. A mild burning immediately after the injection is to be expected. This usually leaves in 10 to 20 seconds. See also WARNINGS and PRECAUTIONS regarding proper method and route of injection.
(2) Systemic Reactions
Most severe systemic reactions usually will begin within a 30-minute time period, but systemic reactions may occur at any time after skin tests or immunotherapy. Symptoms may range from mild to life-threatening from anaphylaxis as described under INDICATIONS AND USAGE. With careful attention to dosage and administration, severe systemic reactions occur infrequently, but it cannot be overemphasized that in sensitive individuals, any injection could result in anaphylactic shock. Therefore, it is imperative that physicians administering allergenic extracts understand and be prepared for the treatment of severe reactions. See CLINICAL PHARMACOLOGY for clinical incidence of systemic reactions and course of action following these reactions.
If a systemic or anaphylactic reaction does occur, apply a tourniquet above the site of injection and inject 1:1000 epinephrine-hydrochloride intramuscularly or subcutaneously into the opposite arm. Loosen the tourniquet at least every 10 minutes. Do not obstruct arterial blood flow with the tourniquet.
EPINEPHRINE DOSAGE
ADULT: 0.3 to 0.5 mL should be injected. Repeat in 5 to 10 minutes if necessary.
PEDIATRIC: The usual initial dose is 0.01 mg (mL) per kg body weight or 0.3 mg (mL) per square meter of body surface area. Suggested dosage for infants to 2 years of age is 0.05 mL to 0.1 mL; for children 2 to 6 years, 0.15 mL; and children 6 to 12 years, 0.2 mL. Single pediatric doses should not exceed 0.3 mg (mL). Doses may be repeated as frequently as every 20 minutes, depending on the severity of the condition and the response of the patient.
After administration of epinephrine, profound shock or vasomotor collapse should be treated with intravenous fluids, and possibly vasoactive drugs. Airway patency should be insured. Oxygen should be given by mask. Intravenous antihistamines, inhaled bronchodilators, theophylline and/or corticosteroids may be used if necessary after adequate epinephrine and circulatory support have been given. Emergency resuscitation measures and personnel trained in their use should be available immediately in the event of a serious systemic or anaphylactic reaction not responsive to the above measures [Ref. J. Allergy and Clinical Immunology, 77(2): p.271-273, 1986].
Rarely are all of the above measures necessary; the tourniquet and epinephrine usually produce prompt responses. However, the physician should be prepared in advance for all contingencies. Promptness in beginning emergency treatment measures is of utmost importance.
For recommendations regarding how to proceed with venom extract dose following systemic reactions, see WARNINGS, PRECAUTIONS and DOSAGE AND ADMINISTRATION sections.
(3) Adverse Event Reporting
Report all adverse events to Jubilant HollisterStier Customer Technical Services Department at 1(800) 992-1120. A voluntary adverse event reporting system for health professionals is available through the FDA MEDWATCH program. Preprinted forms (FDA Form 3500) are available from the FDA by calling 1(800) FDA-1088. Completed forms should be mailed to MEDWATCH, 5600 Fisher Lane, Rockville, MD 20852-9787 or Fax to: 1(800) FDA-0178.

OVERDOSAGE

See ADVERSE REACTIONS.

DOSAGE AND ADMINISTRATION

(1) General
Parenteral drug products should be inspected visually for particulate matter and discoloration prior to administration, whenever solution and container permit. Reconstitute and dilute the freeze-dried venom as directed below. Sterile Albumin Saline with Phenol (0.4%) must be used to reconstitute and dilute the venoms for skin testing and treatment. Reconstitute the freeze-dried venoms by adding 5.5 mL Sterile Albumin Saline with Phenol (0.4%) to the vial using a sterile syringe. Swirl or rock the container to dissolve the venom completely. DO NOT SHAKE, since shaking can cause foaming. Dilutions (see table below) must be made in Sterile Albumin Saline with Phenol (0.4%). They must be made accurately and aseptically, using sterile solution, vials, syringes, etc., and thoroughly mixed by rocking or swirling. DO NOT SHAKE. Maintain stock solutions and dilutions constantly at 2° - 8°C.

Extract of Volume | Extract Concentration |  | Diluent Volume |  | Dilution Concentration
1 part of | 100 µg/mL | + | 9 parts | = | 10 µg/mL
1 part of | 10 µg/mL | + | 9 parts | = | 1 µg/mL
1 part of | 1µg/mL | + | 9 parts | = | 0.1µg/mL
1 part of | 0.1 µg/mL | + | 9 parts | = | 0.01 µg/mL
1 part of | 0.01 µg/mL | + | 9 parts | = | 0.001 µg/mL
1 part of | 0.001 µg/mL | + | 9 parts | = | 0.0001 µg/mL

As an example of the above dilution table:

Extract of Volume | Extract Concentration |  | Diluent Volume |  | Dilution Concentration
0.2mL of | 100 µg/mL | + | 1.8mL | = | 10 µg/mL
0.2mL of | 10 µg/mL | + | 1.8mL | = | 1 µg/mL
0.2mL of | 1 µg/mL | + | 1.8mL | = | 0.1 µg/mL
0.2mL of | 0.1 µg/mL | + | 1.8mL | = | 0.01 µg/mL
0.2mL of | 0.01 µg/mL | + | 1.8mL | = | 0.001 µg/mL
0.2mL of | 0.001 µg/mL | + | 1.8mL | = | 0.0001 µg/mL

NOTE: Mixed Vespid Venom Protein concentrations will be three times that shown above.
(2) Diagnosis
Since the level of insect venom specific IgE may fall to low levels briefly after a reaction to a sting, patients should not be tested until 2 to 4 weeks after any sting.
Skin testing should be carried out with all five individual venoms, since many patients have multiple sensitivities .(4)Mixed Vespid venom protein should be used only for therapy - not for diagnosis. Prick testing should be done before intradermal testing to determine appropriate concentration for intradermal testing. See Intradermal Tests below. Skin testing (prick and intradermal) provides information to assist in identifying those patients who are to be classified as extremely sensitive and who may not tolerate the Suggested Dose Schedule. See DOSAGE AND ADMINISTRATION, Immunotherapy CAUTION.
In both the prick and intradermal tests, a negative control test with diluent alone must be performed. A histamine positive control test is recommended.
The flexor surface of the forearm is the usual location for skin testing. It is important that a separate sterile syringe and needle be used for each extract and each patient.
Prick Tests: Prick tests are accomplished using a solution of 1 µg/mL venom protein, by applying one drop of the 1 µg/mL venom protein solution to the forearm, and by pricking the skin through the surface of the drop with a sterile 27 gauge needle. The prick is superficial and should not draw blood.
Skin response should be assessed after approximately 15-20 minutes.
For prick tests, a positive reaction (reaction greater than diluent control) at the 1 µg/mL concentration indicates a high level of sensitivity to the test venom.
Intradermal Tests: Patients showing a positive reaction to the prick test at the 1 µg/mL concentration should begin intradermal tests at concentrations of not more than 0.0001 to 0.001 µg/mL. Patients with negative prick tests may begin intradermal tests at a concentration of 0.001 µg/mL.
A 1 mL tuberculin syringe with a short 27-gauge needle should be used to deliver a volume of 0.05 mL for intradermal testing. Introduce the needle into the superficial skin layers, bevel down, until the bevel is completely buried, then slowly inject a 0.05 mL aliquot of the venom dilution, making a small bleb.
Start intradermal tests with the most dilute solution. If after 20 minutes no skin reaction is obtained, continue the intradermal testing using ten-fold increments in the concentration until a reaction of 5-10 mm wheal and 11-20 mm erythema is obtained, or until a concentration of 1 µg/mL has been tested, whichever occurs first.
A patient should be considered sensitive to the test venom when a skin response of 5-10 mm wheal and 11-20 mm erythema (or greater) occurs at a concentration of 1 µg/mL or less(8), providing that this reaction is greater than that of the diluent control.
(3) Immunotherapy
For proper method and route of injection, see WARNINGS, PRECAUTIONS and ADVERSE REACTIONS.
The most common site of injection is the lateral aspect of the upper arm. Patients who have multiple venom sensitivities should be given each specific venom injection in a separate site. (Except, if the patient has sensitivities to Yellow Jacket, Yellow Hornet, and White-Faced Hornet venoms concurrently, s/he can be injected with Mixed Vespid venom protein, an equal mixture of these three vespid venoms.) Note which venom preparation is injected at a specific site, so that dosage of that venom preparation can be adjusted if an excessive local reaction occurs. In patients receiving more than one venom, there is theoretically a greater risk of systemic reactions.
CAUTION: Sensitivity to venom differs from patient to patient. Thus, it is not possible to provide a dosage schedule suitable for all patients. The Suggested Dose Schedule shown below was used in clinical trials (4) and should be suitable for a majority of patients.
IN EXTREMELY SENSITIVE PATIENTS, however, an individualized dose schedule must be employed which will be dictated by the patient's sensitivity. This individualized schedule will probably include weaker dilutions and smaller increments between doses in progressing to the maintenance level (100 µg per venom). In identifying those patients to be classified as extremely sensitive, individuals reacting with significant skin test (wheal greater than 5 mm and erythema greater than 20 mm) at intradermal skin test concentrations of 0.01 µg/mL or less, or those patients experiencing a systemic reaction to any venom skin test concentration, should be considered highly sensitive.
Suggested Dose Schedule for a single venom:

Dose No. | *Volume of 1 µg/mL | Dose No. | Volume of 10 µg/mL | Dose No. | Volume of 100 µg/mL
1..... | ...0.05 mL | 5..... | ...0.05 mL | 9..... | ...0.05mL
2..... | ...0.10 mL | 6..... | ...0.10 mL | 10.... | ...0.10mL
3..... | ...0.20 mL | 7..... | ...0.20 mL | 11.... | ...0.20mL
4..... | ...0.40 mL | 8..... | ...0.40 mL | 12.... | ...0.40mL
 |  |  |  | 13.... | ...0.60mL
 |  |  |  | 14.... | ...0.80mL
 |  |  |  | 15.... | ...1.00mL

Mixed Vespid Venom will contain three times the venom protein per mL shown in this table.
*See preceding CAUTION Section.
In proceeding with the Suggested Dose Schedule, or modified schedules (for highly sensitive patients), it is recommended that injections be given at least once per week, as in the clinical studies. (See CLINICAL PHARMACOLOGY and INDICATIONS AND USAGE.) When building the dose, it is important that dose intervals not exceed one week since longer intervals may decrease the patient's tolerance of the extract.
Based on the clinical studies(4), it is suggested that if a systemic, extremely large local (10 cm or more in duration, or other severe local symptoms), or persistent and severe delayed local reaction occurs during the dose building phase, the dose at the next visit should be held constant (or reduced, depending on judgment of the severity of the reaction) as was done at Study Center "A" which reported the least number of systemic reactions during the course of therapy.
It must be considered important to achieve the 100 µg per venom maintenance dose (the maintenance dose for Mixed Vespid venom protein is 300µg), since there are no data on effectiveness of maintenance levels below 100 µg per venom. Following the achievement of maintenance level (100 µg per venom), it is recommended that a second maintenance injection be given at a 1-week interval, and a third maintenance injection at a 2-week interval. Administer the next injection at a 3-week interval, and then monthly for ongoing maintenance.
See CLINICAL PHARMACOLOGY and INDICATIONS AND USAGE for further information regarding clinical studies on which the above recommendations are based. The optimum duration for immunotherapy is not known, so current recommendations are that maintenance injections be continued indefinitely, year around, particularly in patients experiencing life-threatening anaphylaxis after insect stings.

4. PEDIATRIC USE

The dose for the pediatric population is the same as for adults. (See PRECAUTIONS.)

5. GERIATRIC USE

The dose for elderly patients is the same as for adult patients under 65.(23) (See PRECAUTIONS.)

HOW SUPPLIED

Jubilant HollisterStier sterile freeze-dried Hymenoptera Venom Products are supplied in 10 mL vacuum-sealed vials containing 550 micrograms (550 µg) venom protein per vial for the single venoms, and 1650 micrograms (1650 µg) per vial for the Mixed Vespid venom protein product. Reconstituting fluid [Sterile Albumin Saline with Phenol (0.4%)] is available separately. Storage: Store freeze-dried and reconstituted venom product, and venom dilutions, at 2° - 8° C, and keep at this temperature range during office use.

LIMITED WARRANTY

A number of factors beyond our control could reduce the efficacy of this product or even result in an ill effect following its use. These include storage and handling of the product after it leaves our hands, diagnosis, dosage, method of administration and biological differences in individual patients. Because of these factors, it is important that this product be stored properly and that the directions be followed carefully during use. No warranty, express or implied, including any warranty of merchantability or fitness, is made. Representatives of the Company are not authorized to vary the terms or the contents of any printed labeling, including the package insert, for this product except by printed notice from the Company's headquarters. The prescriber and user of this product must accept the terms hereof.

REFERENCES

1. Lockey, Richard F., Linda M. Benedict, Paul C. Turkeltaub, Samuel C. Bukantz. Fatalities from immunotherapy (IT) and skin testing (ST). J. Allergy Clin. Immunol. 79 (4): 660-677, 1987.

2. Jacobs, Robert L., Goeffrey W. Rake, Jr., et. al. Potentiated anaphylaxis in patients with drug-induced beta-adrenergic blockade. J. Allergy Clin. Immunol. 68 (2): 125-127, August 1981.
3. Hunt, K. J., M. D. Valentine, A. K. Sobotka, A. W. Benton, F. J. Amodio, L. M. Lichtenstein. A controlled trial of immunotherapy in insect hypersensitivity. New Eng. J. Med. 299: 157-161, July 27, 1978.
4. Summary of data from BB-IND 1292 clinical studies, 1978-79, on Hollister-Stier products.
5. Amodio, F., L. Markley, M. D. Valentine, A. K. Sobotka, L. M. Lichtenstein. Maintenance immunotherapy for Hymenoptera sensitivity. J. Allergy Clin. Immunol. 61 (3): 134, 1978.
6. Reisman, R. E., Allergy Principles and Practice. E. Middleton, C. E. Reed, E. F. Ellis, ed. C. V. Mosby Co., 1978.
7. Sobotka, A. K., N. F. Adkinson, Jr., M. D. Valentine, L. M. Lichtenstein. Allergy to insect stings. IV. Diagnosis by R.A.S.T. J. Immunol. 121 (6): 2477-2484, 1978.
8. Hunt, K. J., M. D. Valentine, A. K. Sobotka, L. M. Lichtenstein. Diagnosis of allergy to stinging insects by skin testing with Hymenoptera venoms. Annals Int. Med. 85: 56-59, 1976.
9. Annals of Allergy, Asthma and Immunology. Inhibitors of angiotensin II: Potential hazards for patients at risk for anaphylaxis. Editorial. 78: 527-529, June 1997.
10. Pharm. Ind. (Germany). Anaphylactoid reactions in patients treated with ACE inhibitor treatment in combination with desensitization treatment or after insect bites. 56 (9): IX226-227, 1994.
11. Tunon-De-Lara, J. M., et al. ACE inhibitors and anaphylactoid reactions during venom immunotherapy. The Lancet (United Kingdom). 340 (8824): 908, Oct. 10, 1992.
12. Weinstien, A. M., B. D. Dubin, W. K. Podleski, S. L. Spector, R. S. Farr. Asthma and pregnancy. JAMA. 124 (11): 1161-1165, 1979.
13. Reid, M. J., R. F. Lockey, P. C. Turkletaub, T. A. E. Platts-Mills. Survey of fatalities from skin testing and immunotherapy. J. Allergy Clin. Immunol. 92 (1): 6-15, July 1993.
14. Reid, M. J., G. Gurka. Deaths associated with skin testing and immunotherapy. J. Allergy Clin. Immunol. 97 (1) Part 3:231, Abstract 195, January 1996.
15. Thompson, R. A. et al. Report of a WHO/IUIS working group. The current status of allergen immunotherapy (hyposensitization). Allergy. 44: 369-379, 1989.
16. Malling, H.J., B. Weeke, et al. The European Academy of Allergology and Clinical Immunology. Position Papers. Allergy. 48 (Supplement 14): 9-82, 1993.
17. Pipkorn, Ulf. Pharmacological influence of anti-allergic medication on In Vivo allergen testing. Allergy. 43: 81-86, 1988.
18. Andersson, M. U. Pipkorn. Inhibition of the dermal immediate allergic reaction through prolonged treatment with topical glucocorticosteroids. J. Allergy Clin. Immunol. 79 (2): 345-349, February 1987.
19. Rao, Kamineni S., et al. Duration of suppressive effect of tricyclic anti-depressants on histamine induced wheal and flare reactions on human skin. J. Allergy Clin. Immunol. 82: 752-757, November 1988.
20. Pipkorn, Ulf, M. Andersson. Topical dermal anesthesia inhibits the flare but not the wheal response to allergen and histamine in the skin prick test. Clinical Allergy. 17: 307-311, 1987.
21. DuBuske, L. M., C. J. Ling, A. L. Sheffer. Special problems regarding allergy immunotherapy. Immunol. Allergy Clin. North Am. (USA). 12 (1): 145-175, 1992.
22. Graft, D., K. Schuberth, A. Kagey-Sobotka, K. Kwiterovich, Y. Niv, L. Lichtenstein, M. Valentine. Assessment of prolonged venom immunotherapy in children. J. Allergy Clin. Immunol. 80 (2): 162-169, August 1987.
23. Peebles, Ray Stokes, Jr., B. Bochner, Howard J. Zeitz, ed. Anaphylaxis in the elderly. Immunol. Allergy Clin. of North Am. 13 (3): 627-646, August 1993.

Suggested Dosage Chart